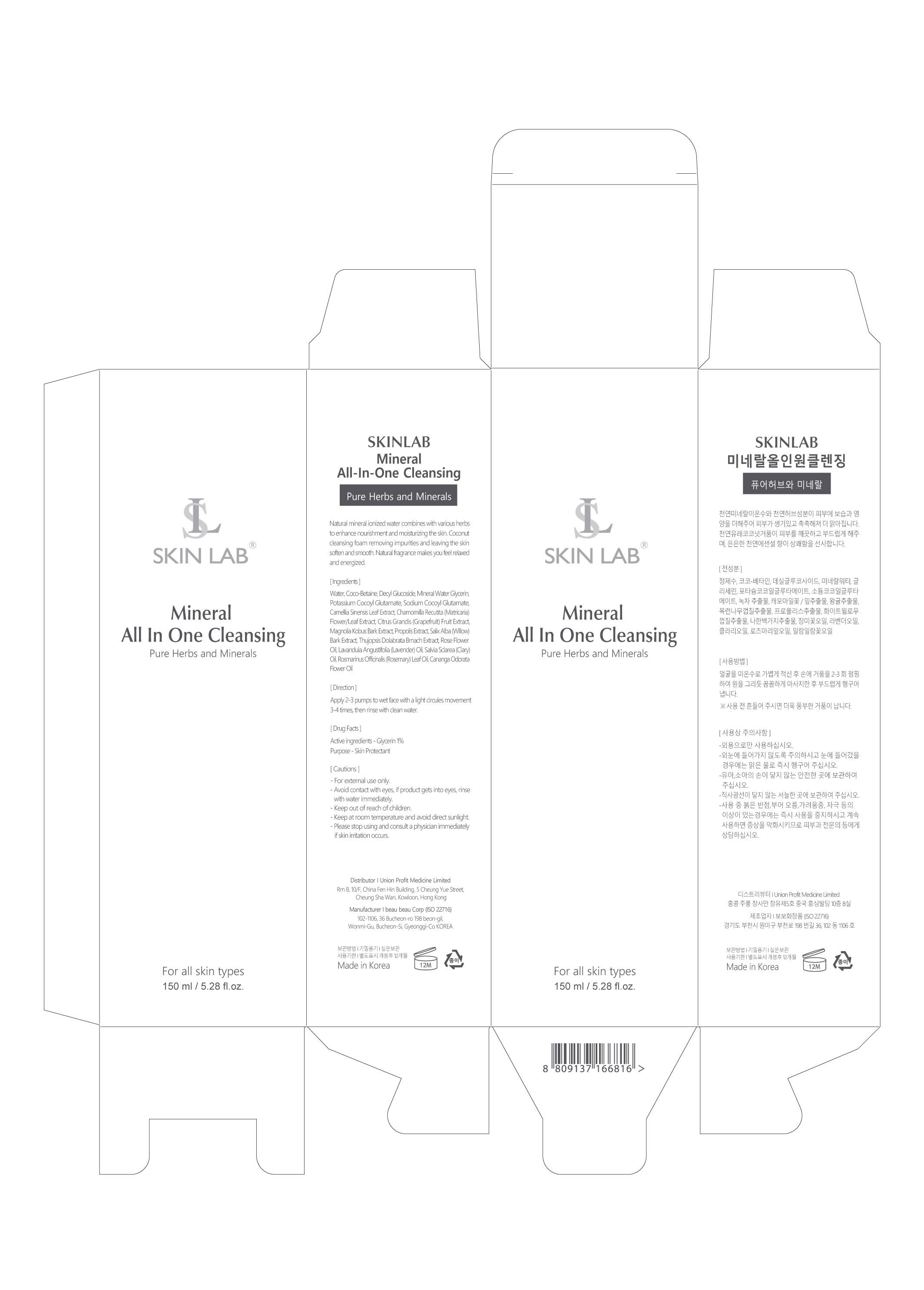 DRUG LABEL: Mineral All-In-One Cleansing
NDC: 73101-005 | Form: LIQUID
Manufacturer: UNION PROFIT MEDICINE LIMITED
Category: otc | Type: HUMAN OTC DRUG LABEL
Date: 20200519

ACTIVE INGREDIENTS: GLYCERIN 1 g/100 g
INACTIVE INGREDIENTS: AVOCADO FRUIT WATER

Direction

Apply 2-3 pumps to wet face with a light circules movement 3-4 times. then rinse with clean water.

Caution

-For external use only.

-Avoid contact with eyes,if product gets into eyes,rinse

with water immediately.

-Keep out of reach of children.

-Keep at room temperature and avoid direct sunlight.

-please stop using and consult a physician immediately if skin irritation occurs.

INDICATIONS AND USAGE

Naturak mineral ionized water combines with various herbs to enhance nourishment and moisturizing the skin coconut cleansing foam removing impurities and leaving the skin sofen and smooth. Natural fragrance makes you feel relaxed and energized.

-Keep out of reach of children.

Purpose-Skin Protectant

drug facts

active ingredients-Glycerin 1%